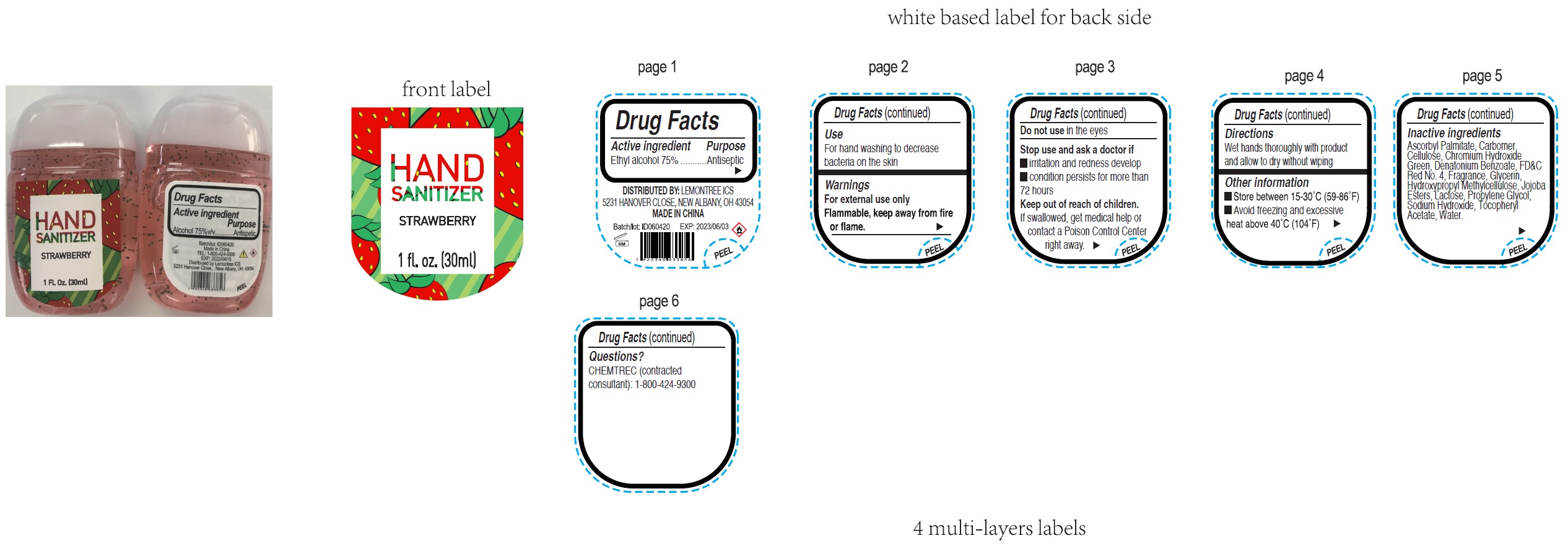 DRUG LABEL: Hand Sanitizer Strawberry
NDC: 79834-104 | Form: GEL
Manufacturer: Lemontree ICS
Category: otc | Type: HUMAN OTC DRUG LABEL
Date: 20200810

ACTIVE INGREDIENTS: ALCOHOL 0.75 mL/1 mL
INACTIVE INGREDIENTS: ASCORBYL PALMITATE; CARBOMER HOMOPOLYMER, UNSPECIFIED TYPE; POWDERED CELLULOSE; CHROMIUM HYDROXIDE GREEN; DENATONIUM BENZOATE; FD&C RED NO. 4; GLYCERIN; HYPROMELLOSE, UNSPECIFIED; LACTOSE, UNSPECIFIED FORM; PROPYLENE GLYCOL; SODIUM HYDROXIDE; .ALPHA.-TOCOPHEROL ACETATE; WATER

Hand Sanitizer, Strawberry

Active ingredient

Ethyl alcohol 75%

Purpose

Antiseptic

Use

For hand washing to decrease bacteria on the skin

Warnings

For external use only

Flammable, keep away from fire or flame

Do not use

in the eyes

Stop use and ask a doctor if

- irritation and redness develop
- condition persists for more than 72 hours

Keep out of reach of children.

If swallowed, get medical help or contact a Poison Control Center right away.

Directions

Wet hands thoroughly with product and allow to dry without wiping

Other information

- Store between 15-30°C (59-86°F)
- Avoid freezing and excessive heat above 40°C (104°F)

Inactive ingredients

Ascorbyl Palmitate, Carbomer, Cellulose, Chromium Hydroxide Green, Denatonium Benzoate, FD&C RedNo. 4, Fragrance, Glycerin, Hydroxypropyl Methylcellulose, Jojoba Esters, Lactose, Propylene Glycol, Sodium Hydroxide, Tocopheryl Acetate, Water.